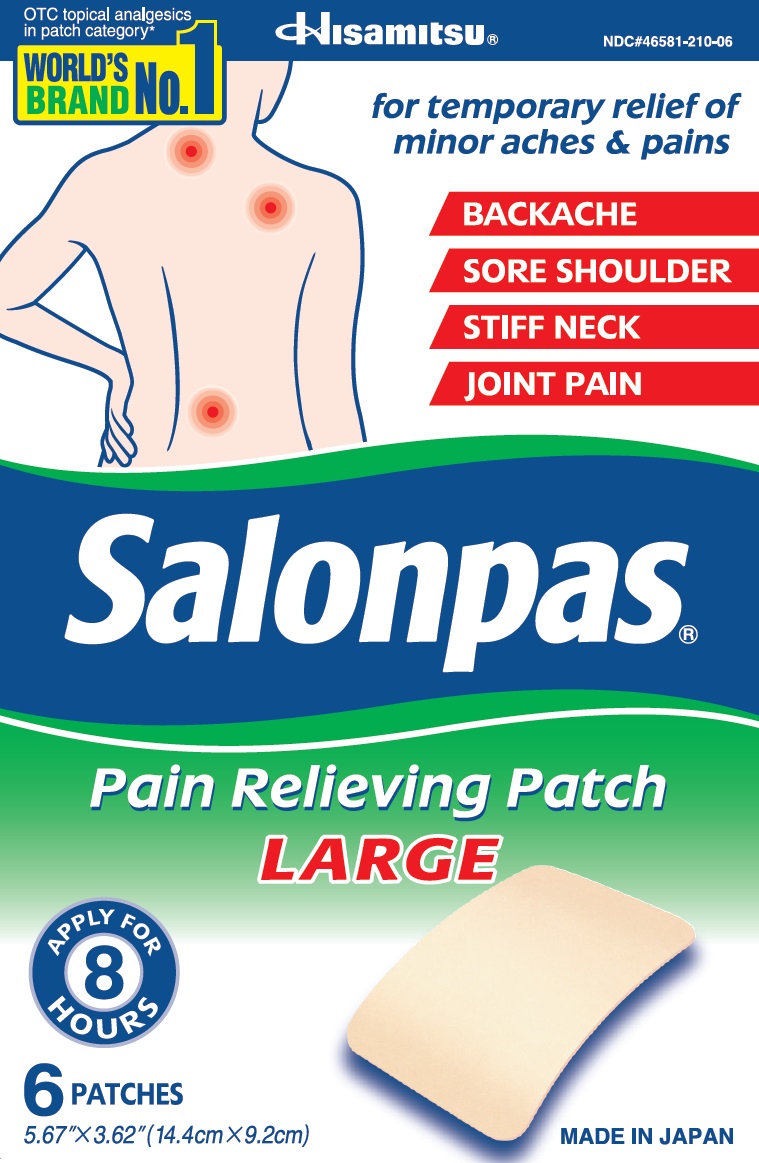 DRUG LABEL: Salonpas
NDC: 46581-210 | Form: PATCH
Manufacturer: Hisamitsu Pharmaceutical Co., Inc.
Category: otc | Type: HUMAN OTC DRUG LABEL
Date: 20241203

ACTIVE INGREDIENTS: CAMPHOR (SYNTHETIC) 86.24 mg/1 1; MENTHOL 166.92 mg/1 1; METHYL SALICYLATE 278.2 mg/1 1
INACTIVE INGREDIENTS: MINERAL OIL; ALUMINUM SILICATE; TITANIUM DIOXIDE

Active ingredients

Camphor 3.1%

Menthol 6.0%

Methyl salicylate 10.0%

Purpose

Topical analgesic

Uses

For temporary relief of minor aches and pains of muscles and joints associated with:

- arthritis
- simple backache
- strains
- bruises
- sprains

Warnings

For external use only

Allergy alert:

If prone to allergic reaction from aspirin or salicylates, consult a doctor before use.

Do not use

- on wounds or damaged skin
- with a heating pad
- if you are allergic to any ingredients of this product

When using this product

- use only as directed
- avoid contact with the eyes, mucous membranes or rashes
- do not bandage tightly

Stop use and ask a doctor if

- rash, itching or excessive skin irritation develops
- contisions worsen
- symptoms persist for more than 7 days
- symptoms clear up and occur again within a few days

If pregnant or breast-feeding,

ask a health professional before use.

Keep out of reach of children.

If swallowed, get medical help or contact a Poison Control Center right away.

Directions

Adults and children 12 years of age and over:

- clean and dry affected area
- remove patch from film
- apply to affected area not more than 3 to 4 times daily
- remove patch from the skin after at most 8-hour application

Children under 12 years of age: consult a doctor

Other information

- avoid storing product in direct sunlight
- protect product from excessive moisture

Inactive ingredients

mineral oil, perfume, polyisobutylene, styrene-isoprene-styrene block copolymer, aluminum silicate, terpene resin, titanium dioxide

Questions or comments?

Toll free 1-800-826-8861 www.salonpas.u

Principal Display Panel

OTC topical analgesics in patch category*
WORLDS'S BRAND NO.1

Hisamitsu

NDC#46581-210-06

for temporary relief of minor aches and pains

BACKACHE
SORE SHOULDER
STIFF NECK
JOINT PAIN

Salonpas

Pain Relieving Patch

LARGE

APPLY FOR 8 HOURS

6 PATCHES

5.67" X 3.62" (14.4 X 9.2cm)

MADE IN JAPAN